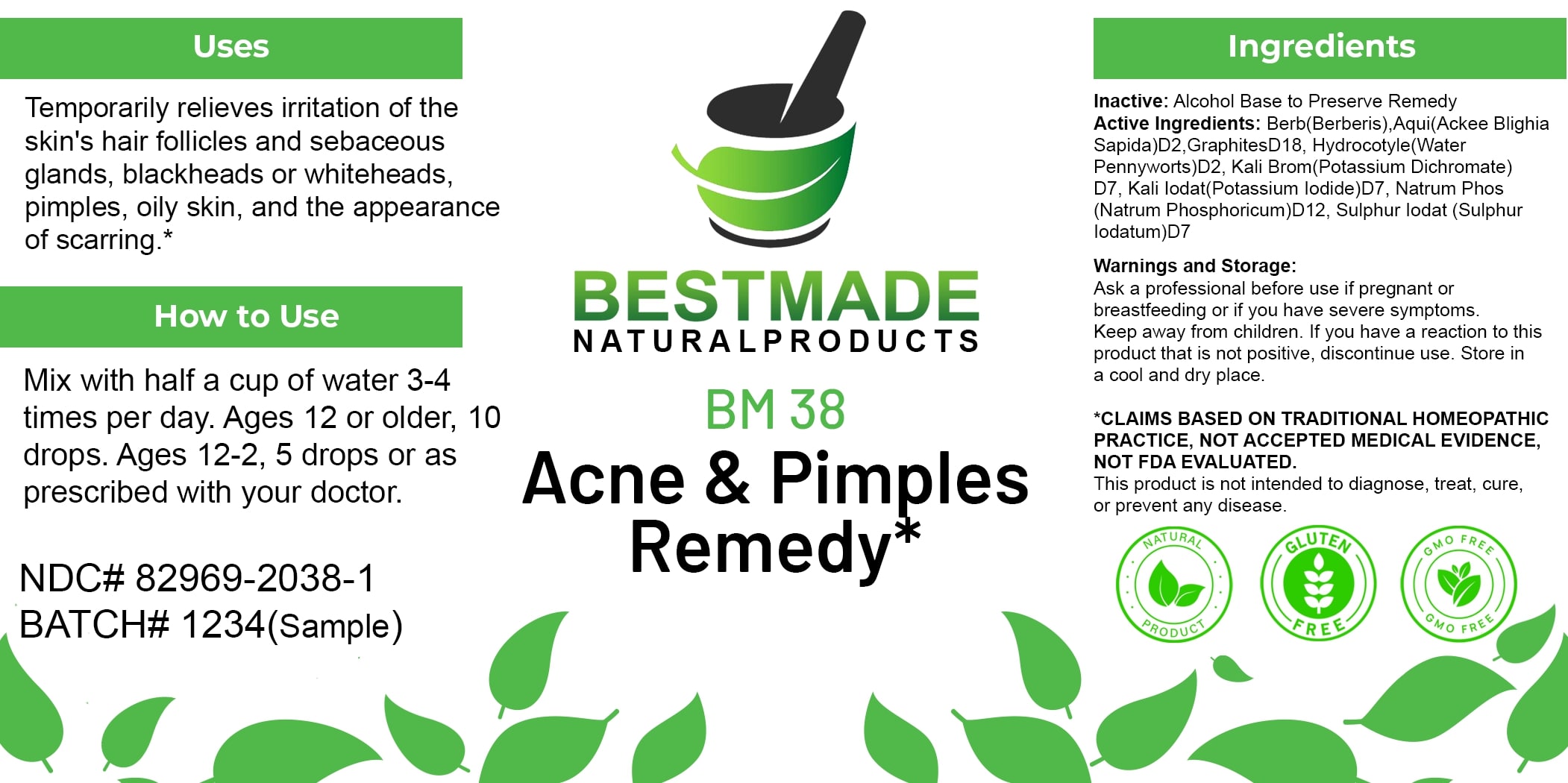 DRUG LABEL: Bestmade Natural Products BM38
NDC: 82969-2038 | Form: LIQUID
Manufacturer: Bestmade Natural Products
Category: homeopathic | Type: HUMAN OTC DRUG LABEL
Date: 20250123

ACTIVE INGREDIENTS: GRAPHITE 30 [hp_C]/30 [hp_C]; SULFUR IODIDE 30 [hp_C]/30 [hp_C]; CENTELLA ASIATICA 30 [hp_C]/30 [hp_C]; POTASSIUM BROMIDE 30 [hp_C]/30 [hp_C]; BERBERIS AQUIFOLIUM ROOT BARK 30 [hp_C]/30 [hp_C]; POTASSIUM IODIDE 30 [hp_C]/30 [hp_C]; SODIUM PHOSPHATE, DIBASIC, HEPTAHYDRATE 30 [hp_C]/30 [hp_C]
INACTIVE INGREDIENTS: ALCOHOL 30 [hp_C]/30 [hp_C]

BM38

DOSAGE AND ADMINISTRATION

How to Use

Mix with half a cup of water 3-4 times per day. Ages 12 or older, 10 drops. Ages 12-2, 5 drops or as prescribed with your doctor.

Uses

Temporarily relieves irritation of the skin's hair follicles and sebaceous glands, blackheads or whiteheads, pimples, oily skin, and the appearance of scarring.*

*CLAIMS BASED ON TRADITIONAL HOMEOPATHIC PRACTICE, NOT ACCEPTED MEDICAL EVIDENCE, NOT FDA EVALUATED.

This product is not intended to diagnose, treat, cure, or prevent any disease.

Uses

Temporarily relieves irritation of the skin's hair follicles and sebaceous glands, blackheads or whiteheads, pimples, oily skin, and the appearance of scarring.*

*CLAIMS BASED ON TRADITIONAL HOMEOPATHIC PRACTICE, NOT ACCEPTED MEDICAL EVIDENCE, NOT FDA EVALUATED.

This product is not intended to diagnose, treat, cure, or prevent any disease.

ACTIVE INGREDIENT

Active Ingredients: Berb(Berberis), Aqui(Ackee Blighia Sapida) D2, Graphites D18, Hydrocotyle(Water Pennyworts) D2, Kali Brom (Potassium Dichromate) D7, Kali lodat(Potassium lodide) D7, Natrum Phos (Natrum Phosphoricum) D12, Sulphur lodat (Sulphur Iodatum) D7

INACTIVE INGREDIENT

Ingredients

Inactive: Alcohol Base to Preserve Remedy

KEEP OUT OF REACH OF CHILDREN

Warnings and Storage:

Ask a professional before use if pregnant or breastfeeding or if you have severe symptoms. Keep away from children. If you have a reaction to this product that is not positive, discontinue use. Store in a cool and dry place.

Warnings and Storage:

Ask a professional before use if pregnant or breastfeeding or if you have severe symptoms. Keep away from children. If you have a reaction to this product that is not positive, discontinue use. Store in a cool and dry place.

*CLAIMS BASED ON TRADITIONAL HOMEOPATHIC PRACTICE, NOT ACCEPTED MEDICAL EVIDENCE, NOT FDA EVALUATED.

This product is not intended to diagnose, treat, cure, or prevent any disease.

Entire package label